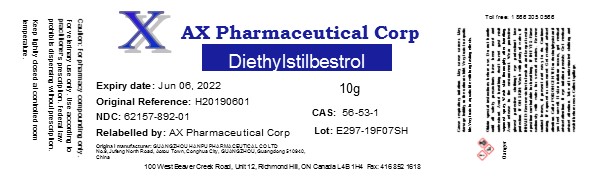 DRUG LABEL: Diethylstilbestrol
NDC: 62157-892 | Form: POWDER
Manufacturer: AX Pharmaceutical Corp
Category: other | Type: BULK INGREDIENT
Date: 20190718

ACTIVE INGREDIENTS: DIETHYLSTILBESTROL 1 g/1 g

Diethylstilbestrol